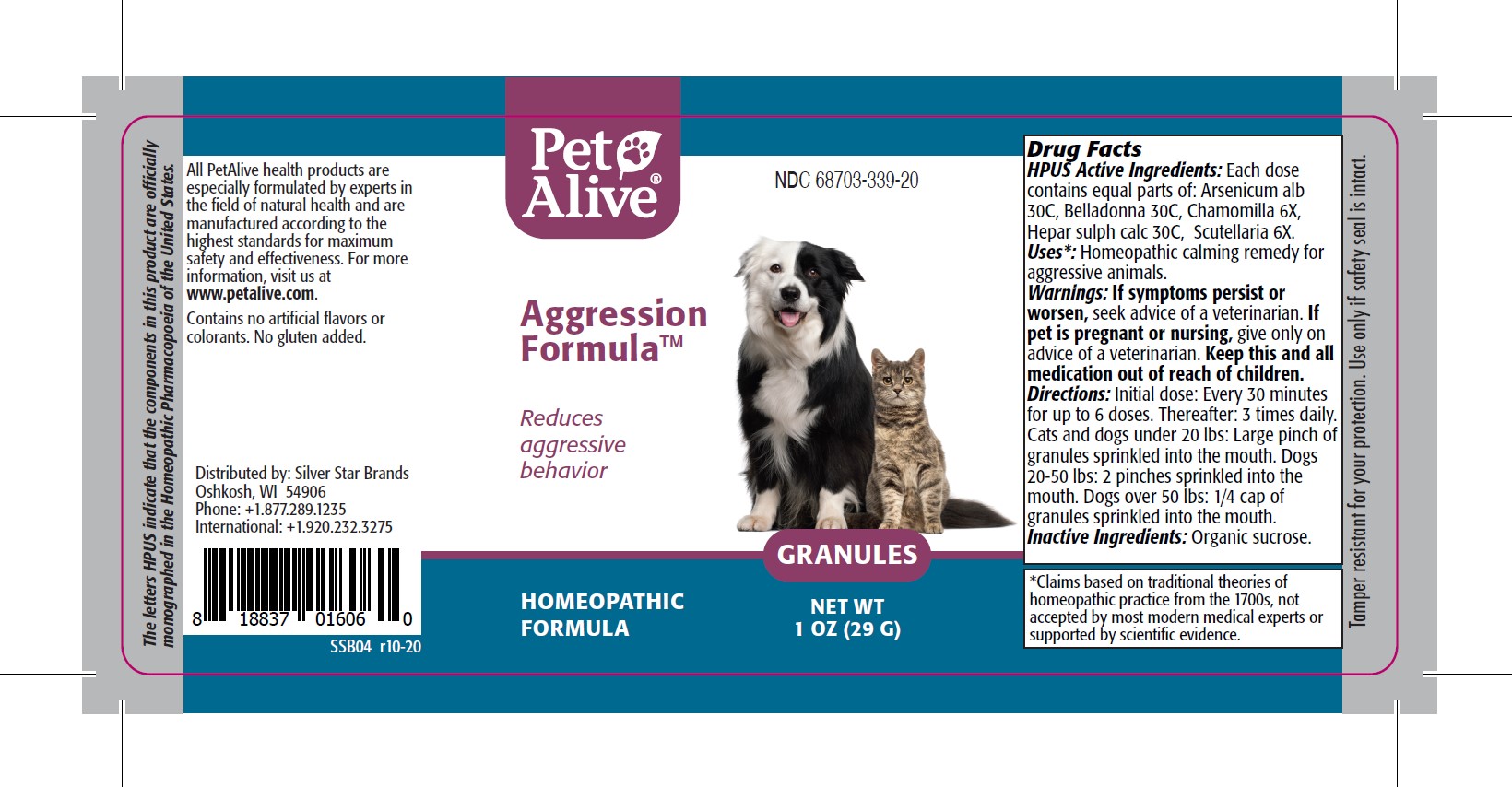 DRUG LABEL: PetAlive Aggression Formula
NDC: 68703-339 | Form: GRANULE
Manufacturer: SILVER STAR BRANDS
Category: homeopathic | Type: OTC ANIMAL DRUG LABEL
Date: 20251216

ACTIVE INGREDIENTS: ARSENIC TRIOXIDE 30 [hp_C]/16 mg; ATROPA BELLADONNA 30 [hp_C]/16 mg; MATRICARIA RECUTITA 6 [hp_X]/16 mg; CALCIUM SULFIDE 30 [hp_C]/16 mg; SCUTELLARIA LATERIFLORA 6 [hp_X]/16 mg
INACTIVE INGREDIENTS: SUCROSE

PetAlive Aggression Formula

PURPOSE

Reduces aggressive behavior

HPUS Active Ingredients:

Arsenicum alb 30C
Belladonna 30C
Chamomilla 6X
Hepar sulph calc 30C
Scutellaria 6X

INDICATIONS AND USAGE

Uses: Homeopathic calming remedy for aggressive animals

WARNINGS

Warnings: If symptoms persist or worsen, seek advise of a veterinarian.

PREGNANCY OR BREAST FEEDING

If pet is pregnant or nursing, give only on advice of a veterinarian.

KEEP OUT OF REACH OF CHILDREN

Keep this and all medication out of reach of children.

DOSAGE AND ADMINISTRATION

Directions: Initial dose: Every 30 minutes for up to 6 doses. Thereafter: 3 times daily. Cats and dogs under 20 lbs: Large pinch of granules sprinkled into the mouth. Dogs 20-50 lbs: 2 pinches sprinkled into the mouth. Dogs over 50 lbs: 1/4 cap of granules sprinkled into the mouth.

Inactive Ingredients: Organic sucrose.

INFORMATION FOR OWNERS/CAREGIVERS

The letters HPUS indicate that the components in this product are officially monographed in the Homeopathic Pharmacopoeia of the United States.

All PetAlive health products are especially formulated by experts in the field of natural health and are manufactured according to the highest standards for maximum safety and effectiveness. For more information, visit us at www.petalive.com.

Contains no artificial flavors or colorants. No gluten added.

Distributed by: Silver Star Brands
Oshkosh, WI 54906
Phone: +1.877.289.1235
International: +1.920.2

STORAGE AND HANDLING

Tamper resistant for your protection. Use only if safety seal is intact.